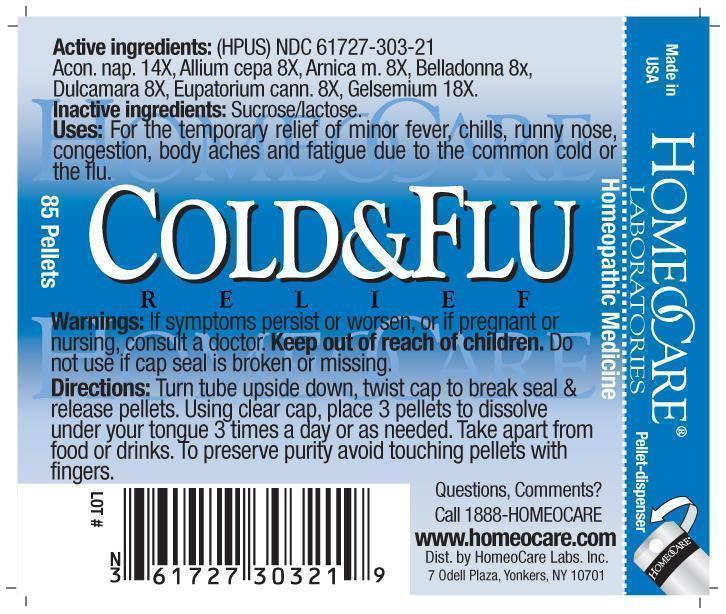 DRUG LABEL: Cold and Flu Relief
NDC: 61727-303 | Form: PELLET
Manufacturer: Homeocare Laboratories
Category: homeopathic | Type: HUMAN OTC DRUG LABEL
Date: 20181226

ACTIVE INGREDIENTS: ACONITUM NAPELLUS 14 [hp_X]/4 g; ONION 8 [hp_X]/4 g; ARNICA MONTANA 8 [hp_X]/4 g; ATROPA BELLADONNA 8 [hp_X]/4 g; SOLANUM DULCAMARA TOP 8 [hp_X]/4 g; EUPATORIUM CANNABINUM FLOWERING TOP 8 [hp_X]/4 g; GELSEMIUM SEMPERVIRENS ROOT 18 [hp_X]/4 g
INACTIVE INGREDIENTS: SUCROSE; LACTOSE

Cold & Flu Relief

Active Ingredients:

Aconitum nap. 14X, Allium cepa 8X, Arnica m. 8X, Belladonna 8X, Dulcamara 8X, Eupatorium cann. 8X, Gelsemium 18X.

Purpose:

For the temporary relief of minor fever, chills, runny nose, congestion, body aches and fatigue due to the common cold or the flu.

Keep out of reach of children.

Indications & Usage:

Turn tube upside down, twist cap to break seal & release pellets. Using clear cap, place 3 pellets to dissolve under your tongue 3 times a day or as needed. Take apart from food or drinks. To preserve purity avoid touching pellets with fingers.

Warnings:

If symptoms persist or worsen, or if pregnant or nursing, consult a doctor. Keep out of reach of children. Do not use if cap seal is broken or missing.

Inactive Ingredients:

Sucrose/lactose.

Dosage & Administration:

Turn tube upside down, twist cap to break seal & release pellets. Using clear cap, place 3 pellets to dissolve under your tongue 3 times a day or as needed. Take apart from food or drinks. To preserve purity avoid touching pellets with fingers.

Cold and Flu Relief

Homeopathic Medicine

85 Pellets

hcl_label_coldflu-2012.jpg